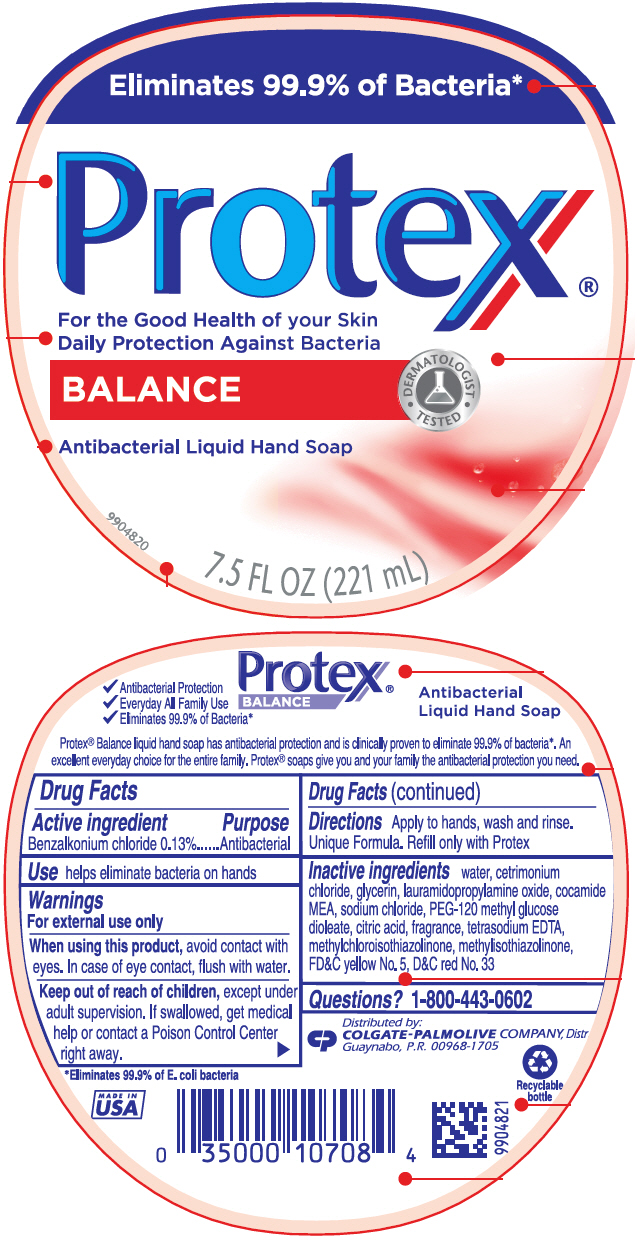 DRUG LABEL: Protex Balance antibacterial hand
NDC: 35000-675 | Form: LIQUID
Manufacturer: COLGATE PALMOLIVE COMPANY
Category: otc | Type: HUMAN OTC DRUG LABEL
Date: 20191210

ACTIVE INGREDIENTS: BENZALKONIUM CHLORIDE 1.33 mg/1 mL
INACTIVE INGREDIENTS: WATER; CETRIMONIUM CHLORIDE; GLYCERIN; LAURAMIDOPROPYLAMINE OXIDE; COCO MONOETHANOLAMIDE; SODIUM CHLORIDE; PEG-120 METHYL GLUCOSE DIOLEATE; CITRIC ACID MONOHYDRATE; EDETATE SODIUM; METHYLCHLOROISOTHIAZOLINONE; METHYLISOTHIAZOLINONE; FD&C YELLOW NO. 5; D&C RED NO. 33

Protex® Balance antibacterial liquid hand soap

Drug Facts

Active ingredient

Benzalkonium chloride 0.13%

Purpose

Antibacterial

Use

helps eliminate bacteria on hands

Warnings

For external use only

When using this product, avoid contact with eyes. In case of eye contact, flush with water.

Keep out of reach of children, except under adult supervision. If swallowed, get medical help or contact a Poison Control Center right away.

Directions

Apply to hands, wash and rinse. Unique Formula. Refill only with Protex

Inactive ingredients

water, cetrimonium chloride, glycerin, lauramidopropylamine oxide, cocamide MEA, sodium chloride, PEG-120 methyl glucose dioleate, citric acid, fragrance, tetrasodium EDTA, methylchloroisothiazolinone, methylisothiazolinone, FD&C yellow No. 5, D&C red No. 33

Questions?

Call toll-free 1-800-443-0602

Distributed by:
COLGATE-PALMOLIVE COMPANY, Distr.
Guaynabo, P.R. 00968-1705

PRINCIPAL DISPLAY PANEL - 221 mL Bottle Label

Eliminates 99.9% of Bacteria*

Protex®

For the Good Health of your Skin
Daily Protection Against Bacteria

BALANCE
• DERMATOLOGIST •
TESTED

Antibacterial Liquid Hand Soap

9904820
7.5 FL OZ (221 mL)